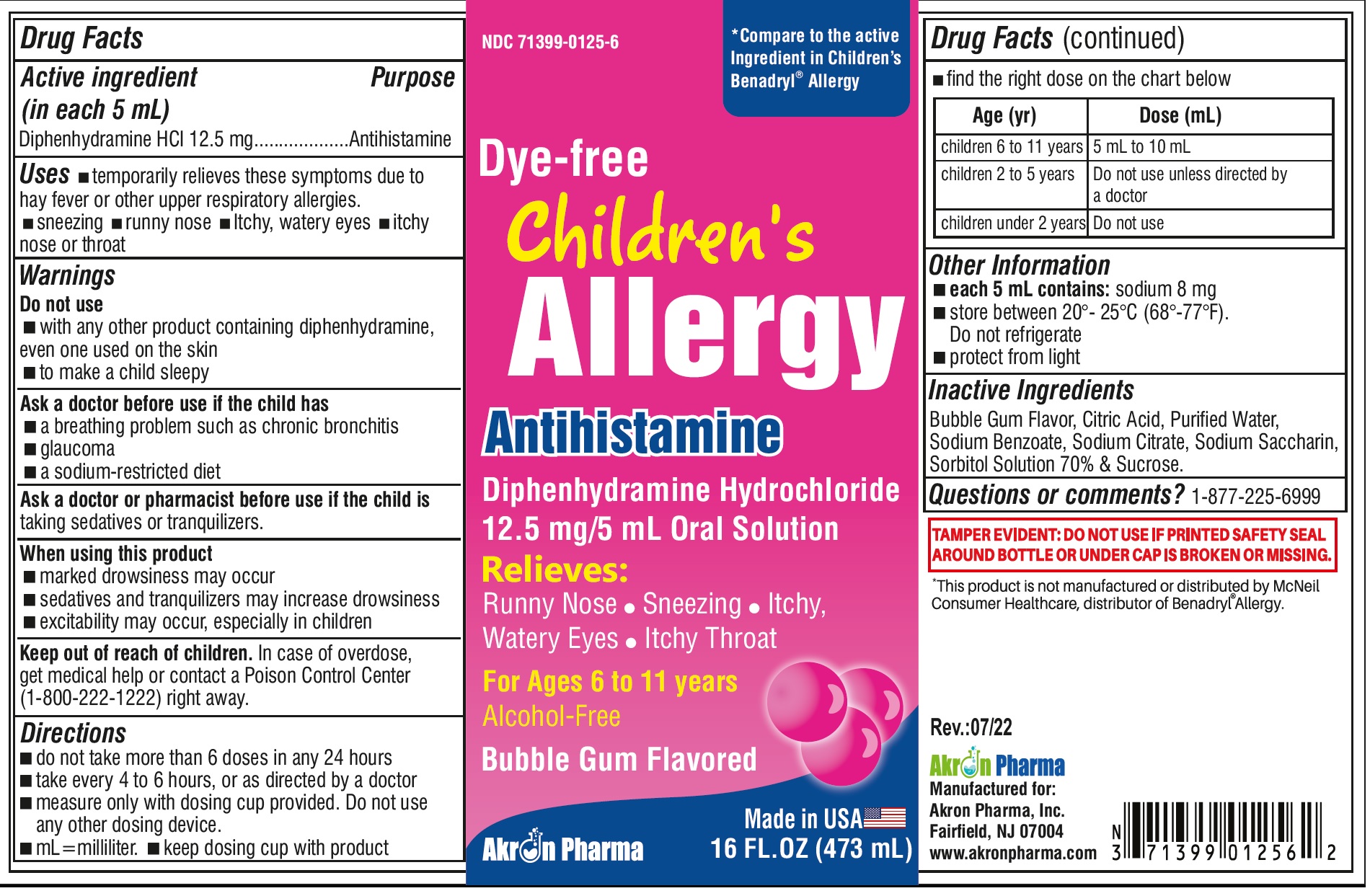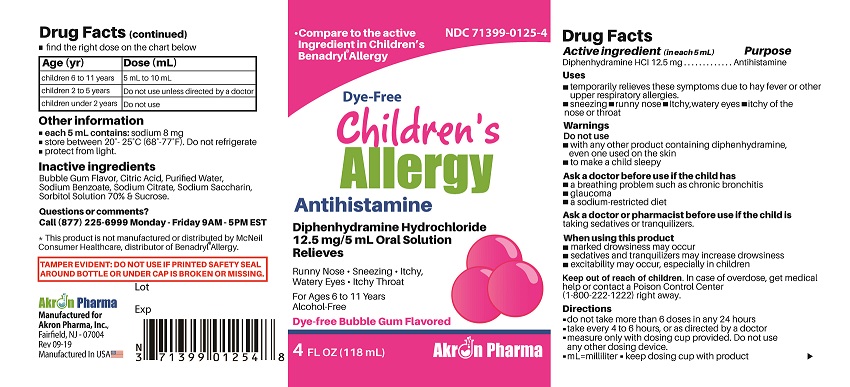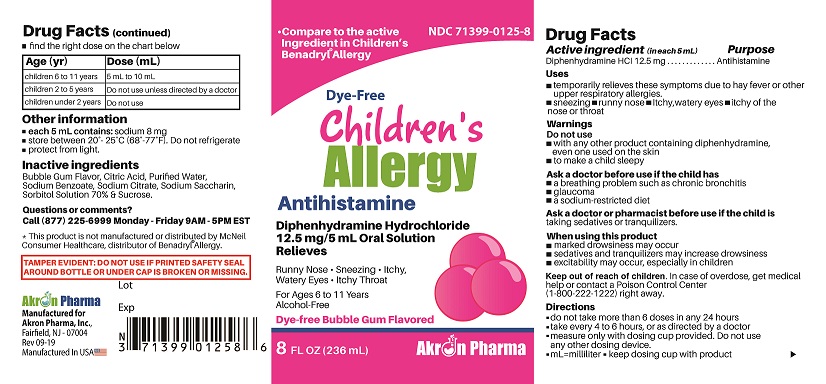 DRUG LABEL: Diphenhydramine HCl
NDC: 71399-0125 | Form: LIQUID
Manufacturer: Akron Pharma Inc.
Category: otc | Type: HUMAN OTC DRUG LABEL
Date: 20230226

ACTIVE INGREDIENTS: DIPHENHYDRAMINE HYDROCHLORIDE 12.5 mg/5 mL
INACTIVE INGREDIENTS: ANHYDROUS CITRIC ACID; WATER; SODIUM BENZOATE; SODIUM CITRATE; SACCHARIN SODIUM; SORBITOL; SUCROSE

Akron Pharma, Inc.

Active ingredient (in each teaspoonful (5 mL))

Diphenhydramine HCl 12.5 mg

Purpose

Antihistamine

Uses

- temporarily relieves these symptoms due to hay fever or other upper respiratory allergies:
  - runny nose
  - sneezing
  - itchy, watery eyes
  - itching of the nose or throat

Warnings

Do not use

- to make a child sleepy
- with any other product containing diphenhydramine, even one used on skin

Ask a doctor before use if you have

- a breathing problem such as emphysema or chronic bronchitis
- glaucoma
- difficulty in urination due to enlargement of the prostate gland

Ask a doctor or pharmacist before use if you are

taking sedatives or tranquilizers.

When using this product

- avoid alcoholic beverages
- alcohol, sedatives, and tranquilizers may increase drowsiness
- excitability may occur, especially in children
- marked drowsiness may occur
- use caution when driving a motor vehicle or operating machinery

If pregnant or breast-feeding,

ask a health professional before use.

Keep out of reach of children.

In case of overdose, get medical help or contact a Poison Control Center (1-800-222-1222) right away.

Directions

- do not take more than 6 doses in 24 hours
- mL = milliliter; FL OZ = fluid ounce
- find right dose on chart below
- take every 4 to 6 hours, or as directed by a doctor

Age | Dose
adults and children 12 years and over | 2 - 4 teaspoonsful (25 mg to 50 mg)
children 6 to 11 years | 1 - 2 teaspoonsful (12.5 mg to 25 mg)
children 2 to 5 years | do not use unless directed by a doctor
children under 2 years | do not use

Other information

- each teaspoonful (5 mL) contains: sodium 5 mg
- store at 25°C (77°F); excursions permitted between 15°-30°C (59°-86°F)
- use by expiration date on package

Inactive ingredients

Bubble Gum Flavor, Citric Acid, Purified Water, Sodium Benzoate, Sodium Citrate, Sodium Saccharin, Sorbitol Solution 70% & Sucrose.

Questions or comments?

Please Call 1(877) 225-6999

Manufactured for:
Akron Pharma, Inc,
Fairfield, NJ 07004
Manufactured in U.S.A